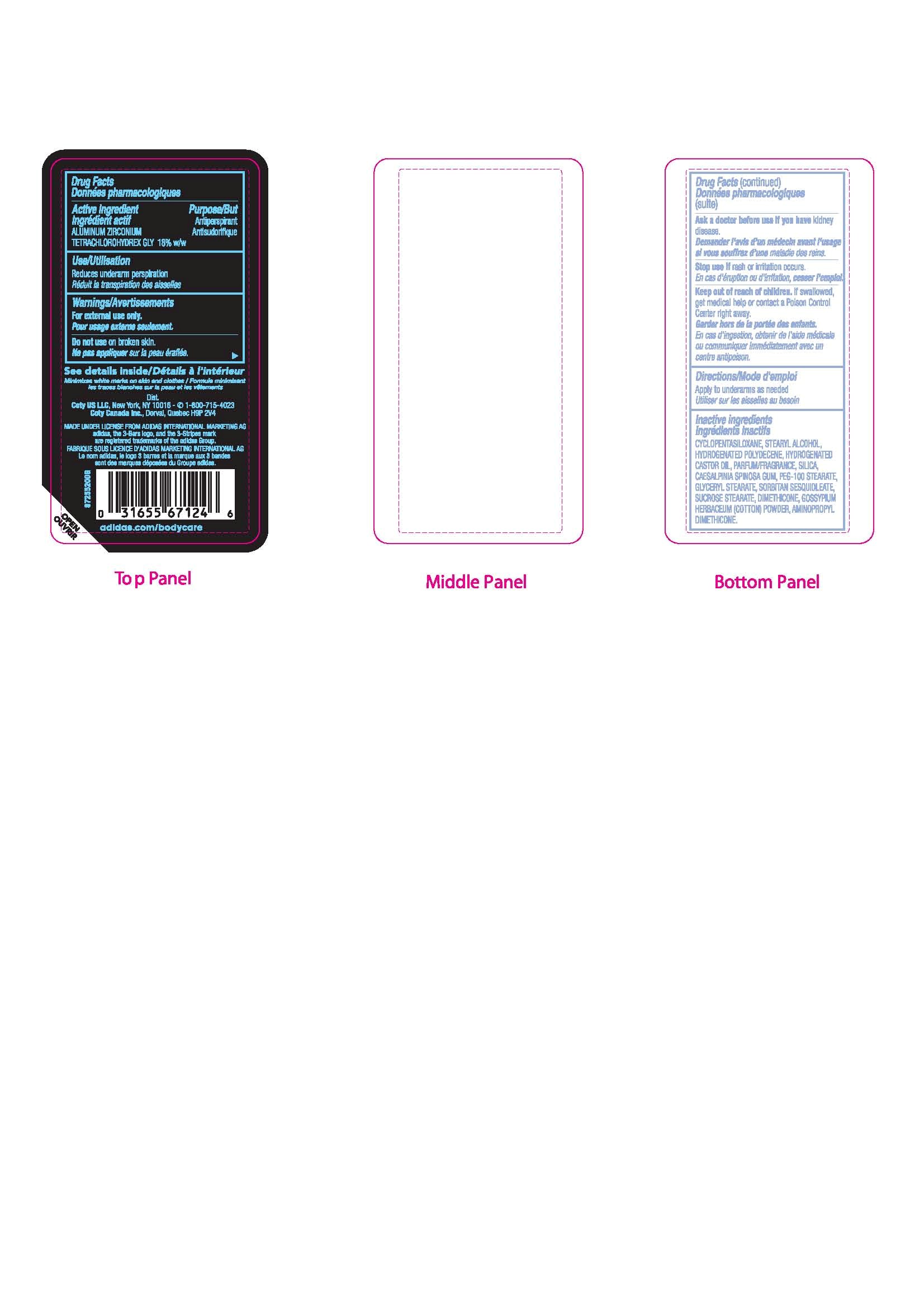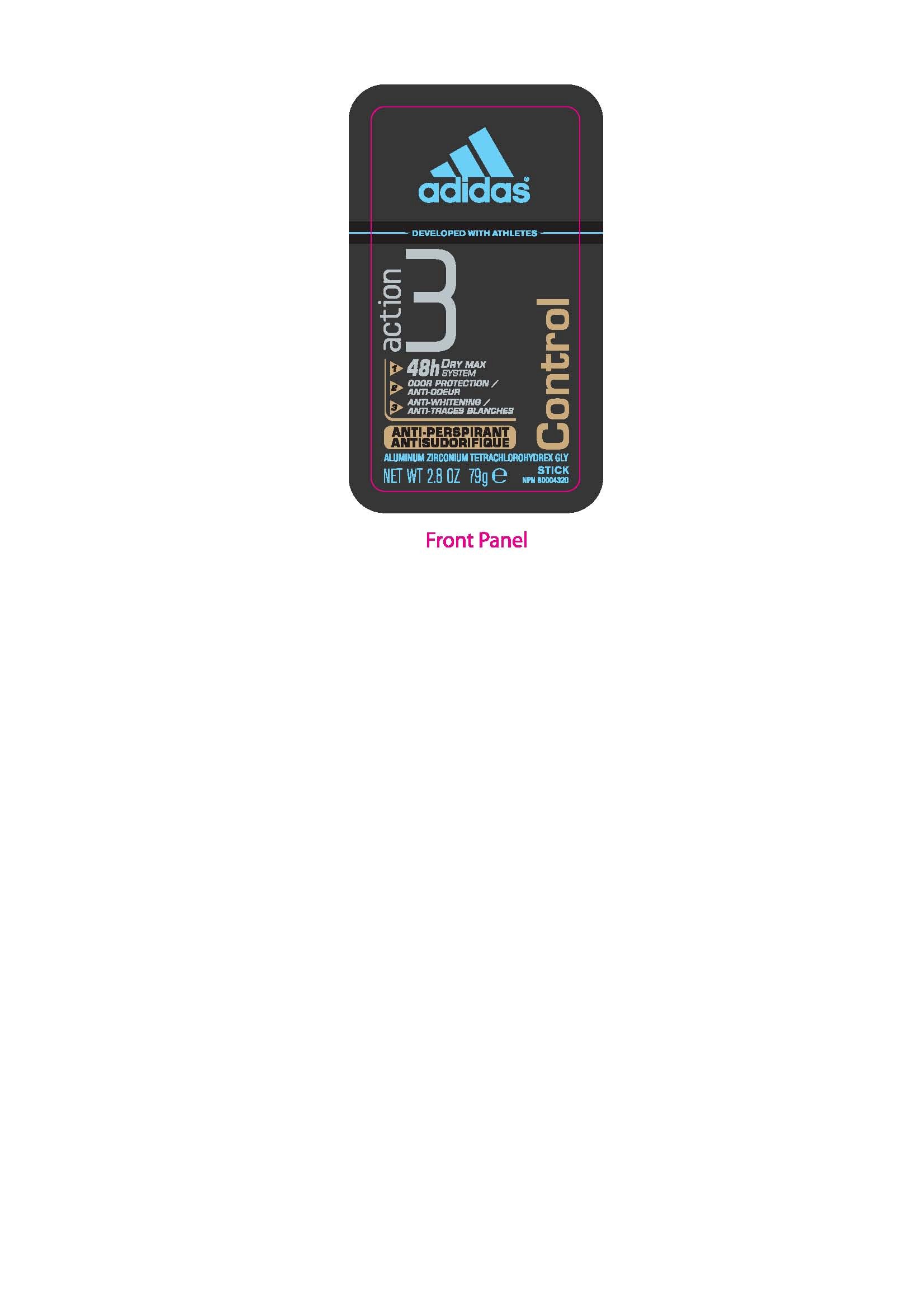 DRUG LABEL: Adidas
NDC: 66184-140 | Form: STICK
Manufacturer: Coty US LLC
Category: otc | Type: HUMAN OTC DRUG LABEL
Date: 20120413

ACTIVE INGREDIENTS: Aluminum Zirconium Tetrachlorohydrex GLY 14.2 g/79 g
INACTIVE INGREDIENTS: CYCLOMETHICONE 5 ; STEARYL ALCOHOL; HYDROGENATED CASTOR OIL ; Silicon Dioxide; CAESALPINIA SPINOSA RESIN; PEG-100 STEARATE; GLYCERYL MONOSTEARATE ; SORBITAN SESQUIOLEATE; SUCROSE STEARATE; DIMETHICONE ; GOSSYPIUM HERBACEUM ROOT BARK

DRUG FACTS

ACTIVE INGREDIENT

Aluminum Zirconium Tetrachlorohydrex GLY 18% w/w

PURPOSE

Antiperspirant

Keep out of reach of children. If swallowed, get medical help or contact a Poison Control Center right away.

INDICATIONS AND USAGE

Reduces underarm perspiration.

WARNINGS

For external use only.

Do not use on broken skin.

Ask a doctor before use if you have kidney disease.

Stop use if rash or irritation occurs.

Keep out of reach of children. If swallowed, get medical help or contact a Poison Control Center right away.

DOSAGE AND ADMINISTRATION

Apply to underarms as needed.

INACTIVE INGREDIENT

Cyclopentasiloxane, Stearyl Alcohol, Hydrogenated Polydecene, Hydrogenated Castor Oil, Parfum/Fragrance, Silica, Caesalpinia Spinosa Gum, PEG-100 Stearate, Glyceryl Stearate, Sorbitan Sesquioleate, Sucrose Stearate, Dimethicone, Gossypium Herbaceum (Cotton) Powder, Aminoporpyl Dimethicone.